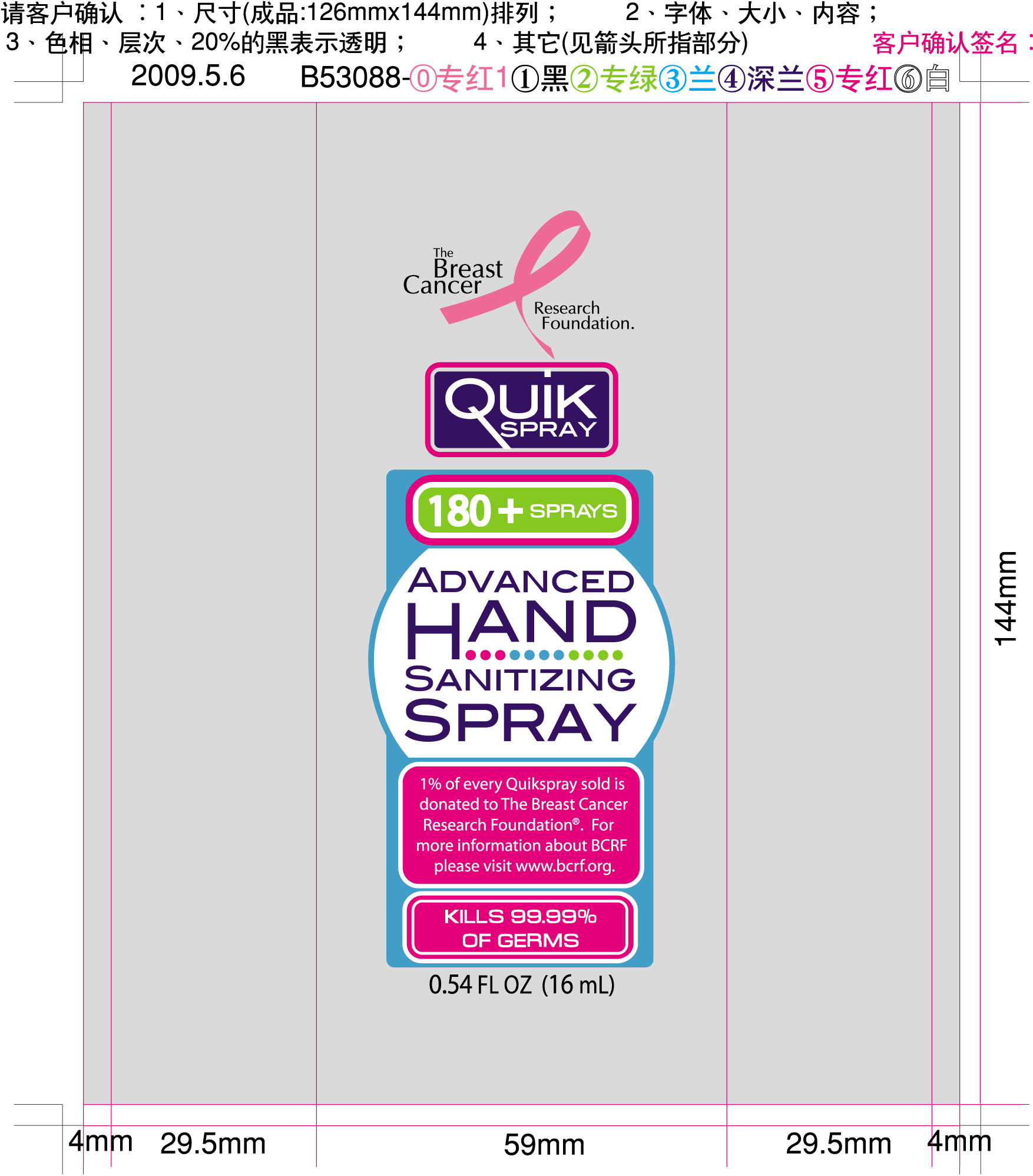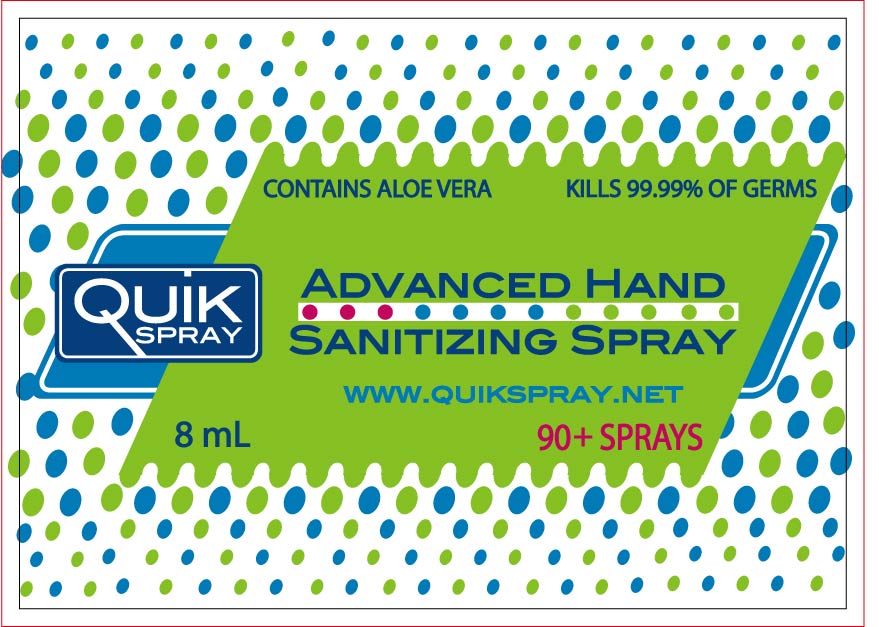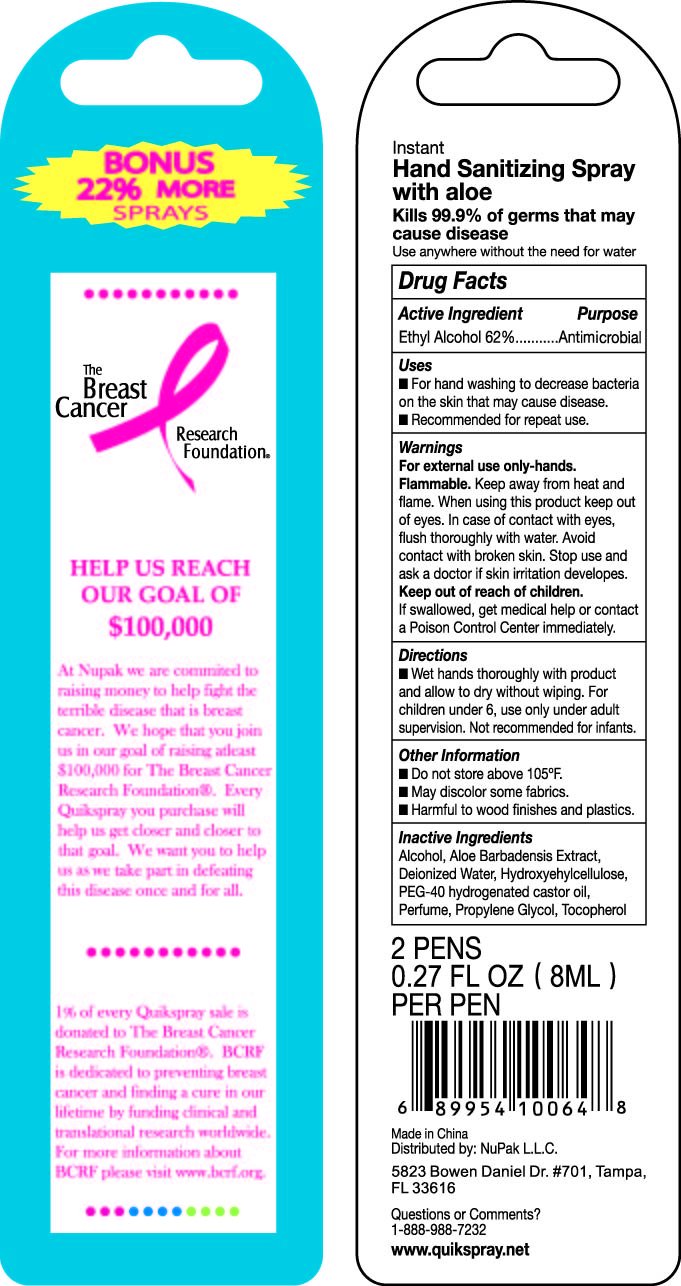 DRUG LABEL: Quik Spray
NDC: 41900-300 | Form: SPRAY
Manufacturer: Cinogen Cosmetics Zhaoqing, LTD.
Category: otc | Type: HUMAN OTC DRUG LABEL
Date: 20090903

ACTIVE INGREDIENTS: ALCOHOL 0.62 mL/1 mL
INACTIVE INGREDIENTS: ALCOHOL; ALOE VERA LEAF; WATER; HYDROXYETHYL CELLULOSE (140 CPS AT 5%); POLYOXYL 40 HYDROGENATED CASTOR OIL; PROPYLENE GLYCOL; ALPHA-TOCOPHEROL

QuikSpray Advanced Hand Sanitizing Spray

DESCRIPTION

Instant

Hand Sanitizing Spray

with Aloe

Kills 99.9 percent of germs that may

cause disease

Use anywhere without the need for water

Drug Facts

Active Ingredient Purpose

Ethyl Alcohol 62 percent Antimicrobial

Uses

For hand washing to decrease bacteria on the skin that may cause disease

Recommended for repeat use

Warnings

For external use only - hands.

Flammable

Keep away from heat and flame. When using this product keep out of eyes.

In case of contact with eyes, flush thoroughly with water.

Avoid contact with broken skin.

Stop use and ask a doctor if skin irritation develops.

Keep out of reach of children.

If swallowed, get medical help or contact a Poison Control Center immediately.

Directions

Wet hands thoroughly with product and allow to dry without wiping.

For children under 6, use only under adult supervision.

Not recommended for infants.

Other Information

Do not store above 105 degrees F.

May discolor some fabrics.

Harmful to wood finishes and plastics.

INACTIVE INGREDIENT

Alcohol , Aloe Barbadensis Extract , Deionized Water , Hydroxyehylcellulose,

PEG 40 hydrogenated castor oil, Perfume , Propylene Glycol , Tocopherol

DESCRIPTION

2 PENS

0.27 FL OZ 8 ML

PER PEN

Made in China

Distributed by NuPak L.L.C

5823 Bowen Daniel Dr 701

Tampa FL 33616

Questions or Comments

1 888 988 7232

www.quikspray.net

DESCRIPTION

The Breast Cancer Research Foundation
Help Us Reach Our Goal Of 100 000
At Nupak we are committed to raising money to help fight the terrible disease that is breast cancer.
We hope that you join us in our goal of raising at least 100 000 for The Breast Cancer Research Foundation.
Every Quikspray you purchase will help us get closer and closer to that goal. We want you to help us as we
take part in defeating this disease once and for all.
1 percent of every Quikspray sale is donated to The Breast Cancer Research Foundation.
BCRF is dedicated to preventing breast cancer and finding a cure in our lifetime by funding clinical
and translational research worldwide.
For more information about BCRF please visit www.bcrf.org

PACKAGE LABEL

The Breast Cancer Research Foundation

Quikspray

180 plus sprays

Advanced Hand Sanitizing Spray

1 percent of every Quikspray sold is donated to The Breast Cancer Research Foundation.

For more information about BCRF please visit www.bcrf.org

Kills 99.99 percent of germs

0.54 FL OZ 16 mL

ASK DOCTOR/PHARMACIST

Quikspray

Contains Aloe Vera

Kills 99.99 percent of germs

Advanced Hand Sanitizing Spray

www.quikspray.net

90 plus sprays

8 mL